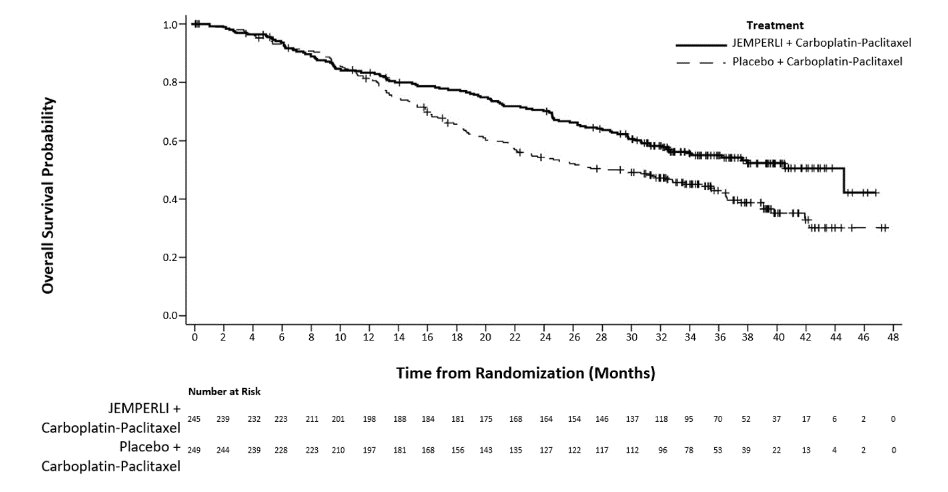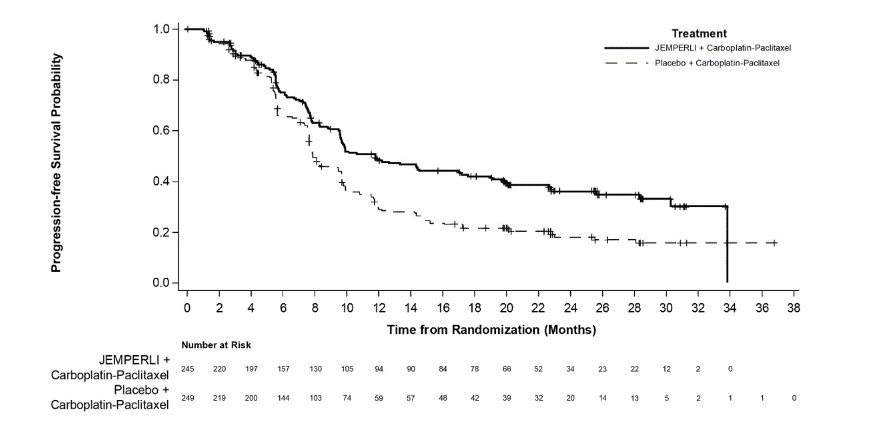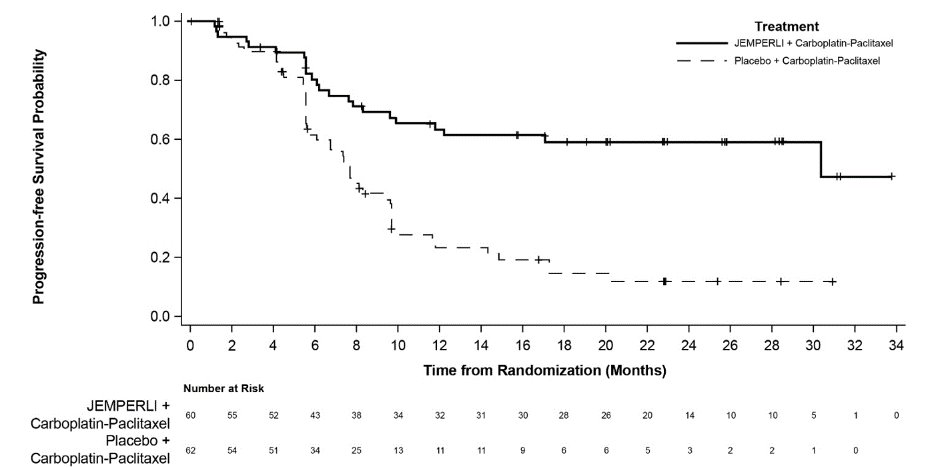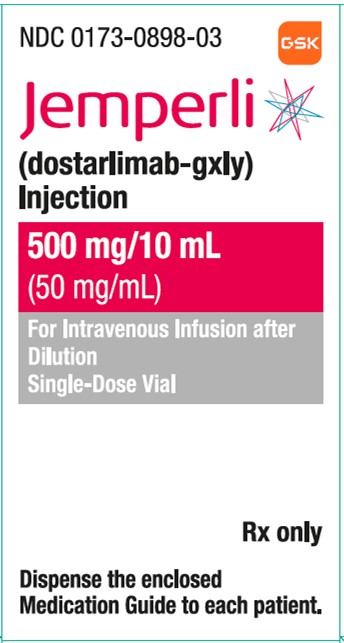 DRUG LABEL: Jemperli
NDC: 0173-0898 | Form: INJECTION
Manufacturer: GlaxoSmithKline LLC
Category: prescription | Type: HUMAN PRESCRIPTION DRUG LABEL
Date: 20250902

ACTIVE INGREDIENTS: DOSTARLIMAB 50 mg/1 mL
INACTIVE INGREDIENTS: CITRIC ACID MONOHYDRATE; ARGININE HYDROCHLORIDE; POLYSORBATE 80; SODIUM CHLORIDE; TRISODIUM CITRATE DIHYDRATE; WATER

HIGHLIGHTS OF PRESCRIBING INFORMATION

These highlights do not include all the information needed to use JEMPERLI safely and effectively. See full prescribing information for JEMPERLI.
JEMPERLI (dostarlimab-gxly) injection, for intravenous use
Initial U.S. Approval: 2021

1 INDICATIONS AND USAGE

JEMPERLI is a programmed death receptor-1 (PD-1)–blocking antibody indicated:

Endometrial Cancer

- in combination with carboplatin and paclitaxel, followed by JEMPERLI as a single agent, for the treatment of adult patients with primary advanced or recurrent endometrial cancer (EC). (1.1)
- as a single agent for the treatment of adult patients with mismatch repair deficient (dMMR) recurrent or advanced EC, as determined by an FDA-approved test, that has progressed on or following prior treatment with a platinum-containing regimen in any setting and are not candidates for curative surgery or radiation. (1.1, 2.1)

Mismatch Repair Deficient Recurrent or Advanced Solid Tumors

- as a single agent for the treatment of adult patients with dMMR recurrent or advanced solid tumors, as determined by an FDA-approved test, that have progressed on or following prior treatment and who have no satisfactory alternative treatment options.^1 (1.2, 2.1)

^1This indication is approved under accelerated approval based on tumor response rate and durability of response. Continued approval for this indication may be contingent upon verification and description of clinical benefit in a confirmatory trial(s). (1.2)

2 DOSAGE AND ADMINISTRATION

- JEMPERLI, in combination with carboplatin and paclitaxel, for primary advanced or recurrent EC: 500 mg every 3 weeks for 6 cycles followed by 1,000 mg monotherapy every 6 weeks for all cycles thereafter. (2.2)
- JEMPERLI, as a single agent, for dMMR recurrent or advanced EC: 500 mg every 3 weeks for 4 cycles followed by 1,000 mg every 6 weeks for all cycles thereafter. (2.2)
- JEMPERLI, as a single agent, for dMMR recurrent or advanced solid tumors: 500 mg every 3 weeks for 4 cycles followed by 1,000 mg every 6 weeks for all cycles thereafter. (2.2)
- Administer as an intravenous infusion over 30 minutes. (2.2)
- For complete dosing instructions, see full prescribing information.

3 DOSAGE FORMS AND STRENGTHS

Injection: 500 mg/10 mL (50 mg/mL) solution in a single-dose vial. (3)

4 CONTRAINDICATIONS

None. (4)

5 WARNINGS AND PRECAUTIONS

- Immune-mediated adverse reactions, which may be severe or fatal, can occur in any organ system or tissue, including the following: immune‑mediated pneumonitis, immune-mediated colitis, immune‑mediated hepatitis, immune-mediated endocrinopathies, immune-mediated nephritis with renal dysfunction, immune‑mediated dermatologic adverse reactions, and solid organ transplant rejection. Monitor for signs and symptoms of immune‑mediated adverse reactions. Evaluate clinical chemistries, including liver enzymes, creatinine, and thyroid function, at baseline and periodically during treatment. Withhold or permanently discontinue JEMPERLI and administer corticosteroids based on the severity of reaction. (2.3, 5.1)
- Infusion-related reactions: Interrupt, slow the rate of infusion, or permanently discontinue JEMPERLI based on severity of reaction. (2.3, 5.2)
- Complications of allogeneic hematopoietic stem cell transplantation (HSCT): Fatal and other serious complications can occur in patients who receive allogeneic HSCT before or after being treated with a PD‑1/PD-L1–blocking antibody. (5.3)
- Embryo-fetal toxicity: Can cause fetal harm. Advise females of reproductive potential of the potential risk to a fetus and to use effective contraception. (5.4, 8.1, 8.3)

6 ADVERSE REACTIONS

- Most common adverse reactions (≥20%), including laboratory abnormalities, with JEMPERLI in combination with carboplatin and paclitaxel in patients with EC are decreased hemoglobin, increased creatinine, peripheral neuropathy, decreased white blood cell count, fatigue, nausea, alopecia, decreased platelets, increased glucose, decreased lymphocytes, decreased magnesium, decreased neutrophils, increased aspartate aminotransferase (AST), arthralgia, rash, constipation, diarrhea, increased alanine aminotransferase (ALT), decreased potassium, decreased albumin, decreased sodium, increased alkaline phosphatase, abdominal pain, dyspnea, decreased appetite, increased amylase, decreased phosphate, urinary tract infection, and vomiting. (6.1)
- Most common adverse reactions (≥20%) with JEMPERLI as a single agent in patients with dMMR solid tumors are fatigue/asthenia, anemia, diarrhea, and nausea. Most common Grade 3 or 4 laboratory abnormalities (≥2%) are decreased lymphocytes, decreased sodium, increased alkaline phosphatase, and decreased albumin. (6.1)

To report SUSPECTED ADVERSE REACTIONS, contact GlaxoSmithKline at 1-888-825-5249 or FDA at 1-800-FDA-1088 or www.fda.gov/medwatch.

8 USE IN SPECIFIC POPULATIONS

Lactation: Advise not to breastfeed. (8.2)

FULL PRESCRIBING INFORMATION

1 INDICATIONS AND USAGE

1.1 Endometrial Cancer

JEMPERLI, in combination with carboplatin and paclitaxel, followed by JEMPERLI as a single agent, is indicated for the treatment of adult patients with primary advanced or recurrent endometrial cancer (EC).

JEMPERLI, as a single agent, is indicated for the treatment of adult patients with mismatch repair deficient (dMMR) recurrent or advanced EC, as determined by an FDA-approved test, that has progressed on or following prior treatment with a platinum-containing regimen in any setting and are not candidates for curative surgery or radiation [see Dosage and Administration (2.1)].

1.2 Mismatch Repair Deficient Recurrent or Advanced Solid Tumors

JEMPERLI, as a single agent, is indicated for the treatment of adult patients with dMMR recurrent or advanced solid tumors, as determined by an FDA-approved test, that have progressed on or following prior treatment and who have no satisfactory alternative treatment options [see Dosage and Administration (2.1)]. This indication is approved under accelerated approval based on tumor response rate and durability of response [see Clinical Studies (14.2)]. Continued approval for this indication may be contingent upon verification and description of clinical benefit in a confirmatory trial(s).

2 DOSAGE AND ADMINISTRATION

2.1 Patient Selection

Single Agent

Select patients for treatment with JEMPERLI as a single agent based on the presence of dMMR in tumor specimens in:

- recurrent or advanced EC [see Clinical Studies (14.1)].
- recurrent or advanced solid tumors [see Clinical Studies (14.2)].

Information on FDA-approved tests for the detection of dMMR status is available at https://www.fda.gov/companiondiagnostics.

Because the effect of prior chemotherapy on test results for dMMR in patients with high-grade gliomas is unclear, it is recommended to test for this marker in the primary tumor specimen obtained prior to initiation of temozolomide chemotherapy in patients with high-grade gliomas.

2.2 Recommended Dosage

The recommended dosage for JEMPERLI is presented in Table 1.

Table 1. Recommended Dosage of JEMPERLI
Indication | Recommended Dosage | Duration/Timing of Treatment
Combination Therapy
Adults with primary advanced or recurrent EC | 500 mga JEMPERLI every 3 weeks for 6 cycles in combination with carboplatin and paclitaxelb followed by; 1,000 mg JEMPERLI as monotherapy every 6 weeks for all cycles thereafter.; Administer JEMPERLI prior to carboplatin and paclitaxel when given on the same day. | Until disease progression, unacceptable toxicity, or up to 3 years.
Monotherapy
Adults with dMMR recurrent or advanced EC and; dMMR recurrent or advanced solid tumors | 500 mga JEMPERLI every 3 weeks for 4 cycles followed by; 1,000 mga JEMPERLI every 6 weeks for all cycles thereafter. | Until disease progression or unacceptable toxicity.
dMMR = Mismatch Repair Deficient; EC = endometrial cancer.
a 30-minute intravenous infusion.
b Refer to the Prescribing Information for the agents administered in combination with JEMPERLI, as appropriate.

2.3 Dosage Modifications for Adverse Reactions

No dose reductions of JEMPERLI are recommended. In general, withhold JEMPERLI for severe (Grade 3) immune‑mediated adverse reactions. Permanently discontinue JEMPERLI for life‑threatening (Grade 4) immune‑mediated adverse reactions, recurrent severe (Grade 3) immune-mediated reactions that require systemic immunosuppressive treatment, or an inability to reduce corticosteroid dose to 10 mg or less of prednisone equivalent per day within 12 weeks of initiating steroids.

Dosage modifications for JEMPERLI for adverse reactions that require management different from these general guidelines are summarized in Table 2.

Table 2. Recommended Dosage Modifications for Adverse Reactions
Adverse Reaction | Severitya | Dosage Modification
Immune-Mediated Adverse Reactions [see Warnings and Precautions (5.1)]
Pneumonitis | Grade 2 | Withholdb
Pneumonitis | Grade 3 or 4 or recurrent Grade 2 | Permanently discontinue
Colitis | Grade 2 or 3 | Withholdb
Colitis | Grade 4 | Permanently discontinue
Hepatitis with no tumor involvement of the liver | AST or ALT increases to more than 3 and up to 8 times ULN; or; Total bilirubin increases to more than 1.5 and up to 3 times ULN | Withholdb
Hepatitis with no tumor involvement of the liver | AST or ALT increases to more than 8 times ULN; or; Total bilirubin increases to more than 3 times ULN | Permanently discontinue
Hepatitis with tumor involvement of the liverc | Baseline AST or ALT is more than 1 and up to 3 times ULN and increases to more than 5 and up to 10 times ULN; or; Baseline AST or ALT is more than 3 and up to 5 times ULN and increases to more than 8 and up to 10 times ULN | Withholdb
Hepatitis with tumor involvement of the liverc | AST or ALT increases to more than 10 times ULN; or; Total bilirubin increases to more than 3 times ULN | Permanently discontinue
Endocrinopathies | Grade 2, 3, or 4 | Withhold until clinically stable or permanently discontinue, depending on severityb
Nephritis with renal dysfunction | Grade 2 or 3 increased blood creatinine | Withholdb
Nephritis with renal dysfunction | Grade 4 increased blood creatinine | Permanently discontinue
Exfoliative dermatologic conditions | Suspected SJS, TEN, or DRESS | Withholdb
Exfoliative dermatologic conditions | Confirmed SJS, TEN, or DRESS | Permanently discontinue
Myocarditis | Grade 2, 3, or 4 | Permanently discontinue
Neurological toxicities | Grade 2 | Withholdb
Neurological toxicities | Grade 3 or 4 | Permanently discontinue
Other Adverse Reactions
Infusion-related reactions [see Warnings and Precautions (5.2)] | Grade 1 or 2 | Interrupt or slow the rate of infusion
Infusion-related reactions [see Warnings and Precautions (5.2)] | Grade 3 or 4 | Permanently discontinue
ALT = alanine aminotransferase; AST = aspartate aminotransferase; DRESS = drug rash with eosinophilia and systemic symptoms; SJS = Stevens-Johnson syndrome; TEN = toxic epidermal necrolysis; ULN = upper limit of normal.
a Based on National Cancer Institute Common Terminology Criteria for Adverse Events, Version 5.0.
b Resume in patients with complete or partial resolution (Grade 0 to 1) after corticosteroid taper. Permanently discontinue if no
complete or partial resolution within 12 weeks of initiating steroids or inability to reduce prednisone to less than 10 mg/day (or
equivalent) within 12 weeks of initiating steroids.
c If AST and ALT are less than or equal to ULN at baseline in patients with liver involvement, withhold or permanently
discontinue JEMPERLI based on recommendations for hepatitis with no liver involvement.

2.4 Preparation and Administration

Preparation for Intravenous Infusion

- Visually inspect the solution for particulate matter and discoloration. The solution is clear to slightly opalescent, colorless to yellow. Discard the vial if visible particles are observed.
- Do not shake.
- JEMPERLI is compatible with an infusion bag made of polyolefin, ethylene vinyl acetate, or polyvinyl chloride with di(2-ethylhexyl) phthalate (DEHP).
- For the 500-mg dose, withdraw 10 mL of JEMPERLI from a vial using a disposable sterile syringe made of polypropylene and dilute into an intravenous infusion bag containing 0.9% Sodium Chloride Injection, USP or 5% Dextrose Injection, USP to a final concentration between 2 to 10 mg/mL (maximum 250 mL).
- For the 1,000-mg dose, withdraw 10 mL from each of 2 vials (withdraw 20 mL total) and dilute into an intravenous bag containing 0.9% Sodium Chloride Injection, USP or 5% Dextrose Injection, USP to a final concentration between 4 to 10 mg/mL (maximum 250 mL).
- Mix diluted solution by gentle inversion. Do not shake.
- Discard any unused portion left in the vial.

Storage of Infusion Solution

Store in the original carton until time of preparation in order to protect from light. The prepared dose may be stored either:

- At room temperature for no more than 6 hours from the time of preparation until the end of infusion.
- Under refrigeration at 2°C to 8°C (36ºF to 46ºF) for no more than 24 hours from time of preparation until end of infusion. If refrigerated, allow the diluted solution to come to room temperature prior to administration.

Discard after 6 hours at room temperature or after 24 hours under refrigeration.

Do not freeze.

Administration

Administer infusion solution intravenously over 30 minutes through an intravenous line using tubing made of polyvinyl chloride or platinum cured silicon; fittings made of polyvinyl chloride or polycarbonate; and a sterile, non-pyrogenic, low‑protein binding, 0.2-micron, in-line or add-on filter.

JEMPERLI must not be administered as an intravenous push or bolus injection. Do not co‑administer other drugs through the same infusion line.

3 DOSAGE FORMS AND STRENGTHS

Injection: 500 mg/10 mL (50 mg/mL) clear to slightly opalescent, colorless to yellow solution in a single-dose vial for intravenous infusion after dilution.

4 CONTRAINDICATIONS

None.

5 WARNINGS AND PRECAUTIONS

5.1 Severe and Fatal Immune-Mediated Adverse Reactions

JEMPERLI is a monoclonal antibody that belongs to a class of drugs that bind to either the programmed death receptor-1 (PD-1) or PD-ligand 1 (PD-L1), blocking the PD-1/PD-L1 pathway, thereby removing inhibition of the immune response, potentially breaking peripheral tolerance, and inducing immune-mediated adverse reactions. Important immune-mediated adverse reactions listed in WARNINGS AND PRECAUTIONS may not include all possible severe and fatal immune‑mediated reactions.

Immune-mediated adverse reactions, which can be severe or fatal, can occur in any organ system or tissue. Immune‑mediated adverse reactions can occur at any time after starting a PD-1/PD-L1–blocking antibody. While immune-mediated adverse reactions usually manifest during treatment with PD-1/PD-L1–blocking antibodies, they can also manifest after discontinuation of PD-1/PD-L1–blocking antibodies.

Early identification and management of immune-mediated adverse reactions are essential to ensure safe use of PD‑1/PD‑L1–blocking antibodies. Monitor closely for symptoms and signs that may be clinical manifestations of underlying immune-mediated adverse reactions. Evaluate liver enzymes, creatinine, and thyroid function tests at baseline and periodically during treatment. In cases of suspected immune-mediated adverse reactions, initiate appropriate workup to exclude alternative etiologies, including infection. Institute medical management promptly, including specialty consultation as appropriate.

Withhold or permanently discontinue JEMPERLI depending on severity [see Dosage and Administration (2.3)]. In general, if JEMPERLI requires interruption or discontinuation, administer systemic corticosteroids (1 to 2 mg/kg/day prednisone or equivalent) until improvement to Grade 1 or less. Upon improvement to Grade 1 or less, initiate corticosteroid taper and continue to taper over at least 1 month. Consider administration of other systemic immunosuppressants in patients whose immune-mediated adverse reaction is not controlled with corticosteroids.

Toxicity management guidelines for adverse reactions that do not necessarily require systemic steroids (e.g., endocrinopathies, dermatologic reactions) are discussed below.

Immune-Mediated Pneumonitis

JEMPERLI can cause immune-mediated pneumonitis, which can be fatal. In patients treated with other PD-1/PD-L1–blocking antibodies, the incidence of pneumonitis is higher in patients who have received prior thoracic radiation.

Immune-mediated pneumonitis occurred in 2.3% (14/605) of patients receiving JEMPERLI, including Grade 2 (1.3%), Grade 3 (0.8%) and Grade 4 (0.2%) pneumonitis. Pneumonitis led to discontinuation of JEMPERLI in 1.3% of patients.

Systemic corticosteroids were required in 79% (11/14) of patients with pneumonitis. Pneumonitis resolved in 11 of the 14 patients. JEMPERLI was withheld for 9 patients. Five patients reinitiated JEMPERLI after symptom improvement; of these, 2 patients had recurrence of pneumonitis.

Immune-Mediated Colitis

JEMPERLI can cause immune-mediated colitis. Cytomegalovirus infection/reactivation have occurred in patients with corticosteroid-refractory immune-mediated colitis treated with PD-1/PD-L1–blocking antibodies. In cases of corticosteroid-refractory colitis, consider repeating infectious workup to exclude alternative etiologies.

Immune-mediated colitis occurred in 1.3% (8/605) of patients receiving JEMPERLI, including Grade 2 (0.7%) and Grade 3 (0.7%) adverse reactions. Colitis led to discontinuation of JEMPERLI in 1 (0.2%) patient.

Systemic corticosteroids were required in 75% (6/8) of patients with colitis. Colitis resolved in 5 of the 8 patients. Of the 4 patients in whom JEMPERLI was withheld for colitis, all reinitiated treatment with JEMPERLI; of these, 1 patient had recurrence of colitis.

Immune-Mediated Hepatitis

JEMPERLI can cause immune-mediated hepatitis, which can be fatal.

Immune-mediated hepatitis occurred in 0.5% (3/605) of patients receiving JEMPERLI, all were Grade 3. Hepatitis led to discontinuation of JEMPERLI in 1 (0.2%) patient. Systemic corticosteroids were required in 2 patients with hepatitis and the events resolved in 2 of the 3 patients.

Immune-Mediated Endocrinopathies

Adrenal Insufficiency: JEMPERLI can cause primary or secondary adrenal insufficiency. For Grade 2 or higher adrenal insufficiency, initiate symptomatic treatment per institutional guidelines, including hormone replacement as clinically indicated. Withhold or permanently discontinue JEMPERLI depending on severity [see Dosage and Administration (2.3)].

Adrenal insufficiency occurred in 1.2% (7/605) patients receiving JEMPERLI, including Grade 2 (0.5%) and Grade 3 (0.7%). Adrenal insufficiency resulted in discontinuation in 1 (0.2%) patient and resolved in 4 of the 7 patients. Of the 4 patients in whom JEMPERLI was withheld for adrenal insufficiency, all reinitiated treatment with JEMPERLI. Systemic corticosteroids were required in 5 of the 7 patients with adrenal insufficiency.

Hypophysitis: JEMPERLI can cause immune-mediated hypophysitis. Hypophysitis can present with acute symptoms associated with mass effect such as headache, photophobia, or visual field cuts. Hypophysitis can cause hypopituitarism. Initiate hormone replacement as clinically indicated. Withhold or permanently discontinue JEMPERLI depending on severity [see Dosage and Administration (2.3)].

JEMPERLI in Combination with Carboplatin and Paclitaxel: Hypophysitis (Grade 3) occurred in 0.4% (1/241) of patients receiving JEMPERLI in combination with carboplatin and paclitaxel. Systemic corticosteroids were required, and the event resolved. JEMPERLI was withheld and the patient reinitiated treatment.

JEMPERLI as a Single Agent: Hypophysitis (Grade 2) occurred in 0.2% (1/605) of patients receiving JEMPERLI as a single agent. Systemic corticosteroids were required, and the event did not resolve. JEMPERLI was withheld and the patient reinitiated treatment.

Thyroid Disorders: JEMPERLI can cause immune-mediated thyroid disorders. Thyroiditis can present with or without endocrinopathy. Hypothyroidism can follow hyperthyroidism. Initiate thyroid hormone replacement or medical management of hyperthyroidism as clinically indicated. Withhold or permanently discontinue JEMPERLI depending on severity [see Dosage and Administration (2.3)].

Thyroiditis: Thyroiditis occurred in 0.5% (3/605) of patients receiving JEMPERLI; all were Grade 2. Systemic corticosteroids were required in 1 of 3 patients and anti-thyroid therapy was required for 2 of 3 patients with thyroiditis. JEMPERLI was withheld for 1 patient and the patient reinitiated treatment. None of the events of thyroiditis resolved; there were no discontinuations of JEMPERLI due to thyroiditis.

Hypothyroidism: JEMPERLI in Combination with Carboplatin and Paclitaxel: Hypothyroidism occurred in 12% (30/241) of patients receiving JEMPERLI in combination with carboplatin and paclitaxel, all of which were Grade 2. Hypothyroidism led to discontinuation of JEMPERLI in 1 patient and resolved in 23% (7/30) of patients. JEMPERLI was withheld for 5 patients and all reinitiated treatment with JEMPERLI. Thyroid hormone replacement was required for 27 of the 30 patients with hypothyroidism.

JEMPERLI as a Single Agent: Hypothyroidism occurred in 8% (46/605) of patients receiving JEMPERLI as a single agent, all of which were Grade 2. Hypothyroidism did not lead to discontinuation of JEMPERLI and resolved in 37% (17/46) of patients. JEMPERLI was withheld for 2 patients and both reinitiated treatment. Thyroid hormone replacement therapy was required for 45 of the 46 patients with hypothyroidism.

Hyperthyroidism: JEMPERLI in Combination with Carboplatin and Paclitaxel: Hyperthyroidism occurred in 3.3% (8/241) of patients receiving JEMPERLI in combination with carboplatin and paclitaxel, including Grade 2 (2.9%) and Grade 3 (0.4%). Hyperthyroidism did not lead to discontinuation of JEMPERLI and resolved in 75% (6/8) of patients. JEMPERLI was withheld for 1 patient and the patient reinitiated treatment. Anti-thyroid therapy was required for 2 of the 8 patients while systemic corticosteroids were required for 1 of the 8 patients with hyperthyroidism.

JEMPERLI as a Single Agent: Hyperthyroidism occurred in 2.3% (14/605) of patients receiving JEMPERLI as a single agent, including Grade 2 (2.1%) and Grade 3 (0.2%). Hyperthyroidism did not lead to discontinuation of JEMPERLI and resolved in 71% (10/14) of the 14 patients. JEMPERLI was withheld for 2 patients and both reinitiated treatment. Anti-thyroid therapy was required for 10 of the 14 patients with hyperthyroidism.

Type 1 Diabetes Mellitus, Which Can Present with Diabetic Ketoacidosis: JEMPERLI can cause type 1 diabetes mellitus, which can present with diabetic ketoacidosis. Monitor patients for hyperglycemia or other signs and symptoms of diabetes. Initiate treatment with insulin as clinically indicated. Withhold or permanently discontinue JEMPERLI depending on severity [see Dosage and Administration (2.3)].

JEMPERLI in Combination with Carboplatin and Paclitaxel: Type 1 diabetes mellitus (Grade 3) occurred in 0.4% (1/241) of patients receiving JEMPERLI in combination with carboplatin and paclitaxel. Type 1 diabetes mellitus led to withholding JEMPERLI; the patient reinitiated treatment and required long-term insulin therapy.

JEMPERLI as a Single Agent: Type 1 diabetes mellitus occurred in 0.2% (1/605) of patients receiving JEMPERLI as a single agent, which was Grade 3. Type 1 diabetes mellitus did not result in treatment discontinuation and did not resolve.

Immune-Mediated Nephritis with Renal Dysfunction

JEMPERLI can cause immune-mediated nephritis, which can be fatal. Nephritis, including tubulointerstitial nephritis, occurred in 0.5% (3/605) of patients receiving JEMPERLI; all were Grade 2. Nephritis led to discontinuation of JEMPERLI in 1 (0.2%) patient and resolved in all patients. JEMPERLI was withheld for 1 patient and the patient reinitiated treatment. Systemic corticosteroids were required in 2 of the 3 patients experiencing nephritis.

Immune-Mediated Dermatologic Adverse Reactions

JEMPERLI can cause immune-mediated rash or dermatitis. Bullous and exfoliative dermatitis, including Stevens-Johnson syndrome (SJS), toxic epidermal necrolysis (TEN), and drug rash with eosinophilia and systemic symptoms (DRESS), have occurred with PD‑1/PD‑L1–blocking antibodies. Topical emollients and/or topical corticosteroids may be adequate to treat mild to moderate non-bullous/exfoliative rashes. Withhold or permanently discontinue JEMPERLI depending on severity [see Dosage and Administration (2.3)].

Other Immune-Mediated Adverse Reactions

The following clinically significant immune-mediated adverse reactions occurred in <1% of the 605 patients treated with JEMPERLI or were reported with the use of other PD-1/PD-L1–blocking antibodies. Severe or fatal cases have been reported for some of these adverse reactions.

Nervous System: Meningitis, encephalitis, myelitis and demyelination, myasthenic syndrome/myasthenia gravis, Guillain‑Barré syndrome, nerve paresis, autoimmune neuropathy.

Cardiac/Vascular: Myocarditis, pericarditis, vasculitis.

Ocular: Uveitis, iritis, other ocular inflammatory toxicities. Some cases can be associated with retinal detachment. Various grades of visual impairment to include blindness can occur. If uveitis occurs in combination with other immune‑mediated adverse reactions, consider a Vogt‑Koyanagi-Harada-like syndrome, as this may require treatment with systemic steroids to reduce the risk of permanent vision loss.

Gastrointestinal: Pancreatitis, including increases in serum amylase and lipase levels, gastritis, duodenitis.

Musculoskeletal and Connective Tissue: Myositis/polymyositis, rhabdomyolysis and associated sequelae including renal failure, arthritis, polymyalgia rheumatica.

Endocrine: Hypoparathyroidism.

Other (Hematologic/Immune): Autoimmune hemolytic anemia, aplastic anemia, hemophagocytic lymphohistiocytosis, systemic inflammatory response syndrome, histiocytic necrotizing lymphadenitis (Kikuchi lymphadenitis), sarcoidosis, immune thrombocytopenia, solid organ transplant rejection, other transplant (including corneal graft) rejection.

5.2 Infusion-Related Reactions

Severe or life-threatening infusion-related reactions have been reported with PD-1/PD-L1–blocking antibodies. Severe infusion-related reactions (Grade 3) occurred in 0.2% (1/605) of patients receiving JEMPERLI. All patients recovered from the infusion-related reactions.

Monitor patients for signs and symptoms of infusion-related reactions. Interrupt or slow the rate of infusion or permanently discontinue JEMPERLI based on severity of reaction [see Dosage and Administration (2.3)].

5.3 Complications of Allogeneic HSCT

Fatal and other serious complications can occur in patients who receive allogeneic hematopoietic stem cell transplantation (HSCT) before or after being treated with a PD-1/PD-L1–blocking antibody. Transplant-related complications include hyperacute graft-versus-host disease (GVHD), acute GVHD, chronic GVHD, hepatic veno-occlusive disease after reduced intensity conditioning, and steroid-requiring febrile syndrome (without an identified infectious cause). These complications may occur despite intervening therapy between PD-1/PD-L1 blockade and allogeneic HSCT.

Follow patients closely for evidence of transplant-related complications and intervene promptly. Consider the benefit versus risks of treatment with a PD-1/PD-L1–blocking antibody prior to or after an allogeneic HSCT.

5.4 Embryo-Fetal Toxicity

Based on its mechanism of action, JEMPERLI can cause fetal harm when administered to a pregnant woman. Animal studies have demonstrated that inhibition of the PD-1/PD-L1 pathway can lead to increased risk of immune-mediated rejection of the developing fetus, resulting in fetal death. Advise pregnant women of the potential risk to a fetus. Advise females of reproductive potential to use effective contraception during treatment with JEMPERLI and for 4 months after the last dose [see Use in Specific Populations (8.1, 8.3)].

6 ADVERSE REACTIONS

The following clinically significant adverse reactions are described elsewhere in the labeling:

- Severe and fatal immune-mediated adverse reactions [see Warnings and Precautions (5.1)]
- Infusion-related reactions [see Warnings and Precautions (5.2)]

6.1 Clinical Trials Experience

Because clinical trials are conducted under widely varying conditions, adverse reaction rates observed in the clinical trials of a drug cannot be directly compared with rates in the clinical trials of another drug and may not reflect the rates observed in practice.

The safety population described in the Warnings and Precautions for use of JEMPERLI in combination with carboplatin and paclitaxel was evaluated in 241 patients with primary advanced or recurrent EC in the randomized, double-blind, active-controlled RUBY trial.

Additionally, the pooled safety population described in Warnings and Precautions reflects exposure to JEMPERLI as a single agent in 605 patients with advanced or recurrent solid tumors in the non-randomized, open-label, multicohort GARNET trial that enrolled 314 patients with EC and 291 patients with other solid tumors. JEMPERLI was administered intravenously at doses of 500 mg every 3 weeks for 4 cycles followed by 1,000 mg every 6 weeks until disease progression or unacceptable toxicity. Among the 605 patients, 32% were exposed for >1 year and 19% were exposed for >2 years.

Primary Advanced or Recurrent Endometrial Cancer: JEMPERLI in Combination with Carboplatin and Paclitaxel

The safety of JEMPERLI in patients with primary advanced or recurrent EC was evaluated in RUBY [see Clinical Studies (14.1)]. Patients received JEMPERLI 500 mg (n = 241) or placebo (n = 246) in combination with carboplatin and paclitaxel every 3 weeks for 6 cycles followed by JEMPERLI 1,000 mg or placebo every 6 weeks until disease progression or unacceptable toxicity. Among the 241 patients, 38.6% were exposed for >1 year and 24.1% were exposed for >2 years.

Serious adverse reactions occurred in 39% of patients receiving JEMPERLI in combination with carboplatin and paclitaxel; the most common serious adverse reactions were sepsis, including urosepsis (3.7%), and pulmonary embolism (3.3%). Fatal adverse reactions occurred in 1.2% of patients receiving JEMPERLI including septic shock (0.8%) and myelosuppression (0.4%).

In patients receiving JEMPERLI in combination with carboplatin and paclitaxel, JEMPERLI was permanently discontinued due to adverse reactions in 46 patients (19%). Adverse reactions that required permanent discontinuation in ≥2 patients included 3 cases (1.2%) of rash maculo-papular, and 2 cases (0.8%) each of increased alanine aminotransferase (ALT), increased aspartate aminotransferase (AST), diarrhea, pancreatitis, fatigue, pneumonitis, and arthralgia.

Dosage interruptions due to an adverse reaction occurred in 37% of patients who received JEMPERLI in combination with carboplatin and paclitaxel. Adverse reactions that required dosage interruption in ≥5% of patients who received JEMPERLI in combination with carboplatin and paclitaxel were anemia, thrombocytopenia, and peripheral neuropathy.

The most common adverse reactions, including laboratory abnormalities (≥20%), were decreased hemoglobin, increased creatinine, peripheral neuropathy, decreased white blood cell count, fatigue, nausea, alopecia, decreased platelets, increased glucose, decreased lymphocytes, decreased magnesium, decreased neutrophils, increased AST, arthralgia, rash, constipation, diarrhea, increased ALT, decreased potassium, decreased albumin, decreased sodium, increased alkaline phosphatase, abdominal pain, dyspnea, decreased appetite, increased amylase, decreased phosphate, urinary tract infection, and vomiting.

Table 3 summarizes the adverse reactions that occurred in ≥20% of patients with primary advanced or recurrent EC receiving JEMPERLI in combination with carboplatin and paclitaxel in RUBY.

Table 3. Adverse Reactions (≥20%) in Patients with Endometrial Cancer Who Received JEMPERLI with Carboplatin and Paclitaxel in RUBY
Adverse Reaction | JEMPERLI with Carboplatin and Paclitaxel; N = 241 |  | Placebo withCarboplatin and Paclitaxel; N = 246
Adverse Reaction | All Grades; % | Grade 3 or 4; % | All Grades; % | Grade 3 or 4; %
Nervous System Disorders
Peripheral neuropathya | 64 | 4.1 | 61 | 2.0
General
Fatigueb | 56 | 3.3 | 63 | 5
Gastrointestinal Disorders
Nausea | 54 | 2.9 | 46 | 1.6
Constipation | 35 | 0.4 | 36 | 0
Diarrhea | 32 | 1.7 | 29 | 0.8
Abdominal painc | 24 | 2.5 | 29 | 2
Vomiting | 20 | 1.7 | 20 | 1.6
Skin and Subcutaneous Tissue
Alopecia | 54 | 0 | 50 | 1.2
Rashd | 37 | 7 | 18 | 1.2
Musculoskeletal and Connective Tissue
Arthralgia | 37 | 1.2 | 35 | 0.4
Respiratory, Thoracic and Mediastinal Disorders
Dyspneae | 23 | 1.7 | 26 | 0.8
Metabolism and Nutrition Disorders
Decreased appetite | 22 | 2.1 | 18 | 0.4
Infections and Infestations
Urinary tract infectionf | 21 | 3.3 | 18 | 1.6
Graded per National Cancer Institute Common Terminology Criteria for Adverse Events Version 4.03.
a Includes neuropathy peripheral and peripheral sensory neuropathy.
b Includes fatigue and asthenia.
c Includes abdominal pain, abdominal pain upper, abdominal pain lower, gastrointestinal pain, abdominal discomfort, epigastric discomfort, and abdominal tenderness.
d Includes rash, rash maculo-papular, palmar-plantar erythrodysesthesia syndrome, rash pustular, skin exfoliation, and vulvovaginal rash.
e Includes dyspnea and dyspnea exertional.
f Includes urinary tract infection, urinary tract infection bacterial, cystitis, and pyelonephritis.

Clinically relevant adverse reactions in <20% of patients with primary advanced or recurrent EC who received JEMPERLI in combination with carboplatin and paclitaxel included:

Endocrine Disorders: Hypothyroidism, hyperthyroidism, thyroiditis, adrenal insufficiency.

Eye Disorders: Keratitis, uveitis.

Gastrointestinal Disorders: Colitis, pancreatitis.

Metabolism and Nutrition Disorders: Type 1 diabetes mellitus.

Musculoskeletal and Connective Tissue Disorders: Immune-mediated arthritis.

Respiratory, Thoracic, and Mediastinal Disorders: Pneumonitis.

Cardiac Disorders: Myocarditis.

Nervous System Disorders: Encephalopathy.

Vascular Disorders: Hypertension, hemorrhage.

Table 4 summarizes the laboratory abnormalities in patients with primary advanced or recurrent EC receiving JEMPERLI in combination with carboplatin and paclitaxel in RUBY.

Table 4. Select Laboratory Abnormalities that Worsened from Baseline Occurring in ≥20% of Patients with Endometrial Cancer Receiving JEMPERLI with Carboplatin and Paclitaxel in RUBY
Laboratory Test | JEMPERLI with Carboplatin and Paclitaxel; N = 241 |  | Placebo with Carboplatin and Paclitaxel; N = 246
Laboratory Test | All Gradesa; % | Grade 3 or 4a; % | All Gradesa; % | Grade 3 or 4a; %
Hematology
Decreased hemoglobin | 79 | 14 | 83 | 16
Decreased white blood cell count | 62 | 13 | 58 | 11
Decreased platelet count | 48 | 4.1 | 48 | 7
Decreased lymphocytes | 44 | 14 | 39 | 13
Decreased neutrophils | 42 | 14 | 52 | 18
Chemistry
Increased creatinine | 75 | 1.7 | 82 | 0.4
Increased glucose | 47 | 10 | 44 | 10
Increased AST | 38 | 3.3 | 23 | 1.6
Increased ALT | 30 | 2.5 | 19 | 0.8
Decreased albumin | 29 | 0.8 | 21 | 0
Increased alkaline phosphatase | 28 | 1.7 | 22 | 0.4
Increased amylase | 21 | 5 | 11 | 1.6
Electrolytes
Decreased magnesium | 44 | 2.1 | 47 | 2
Decreased potassium | 30 | 6 | 29 | 4.1
Decreased sodium | 29 | 6 | 22 | 3.7
Decreased phosphate | 21 | 1.2 | 18 | 3.7
ALT = alanine aminotransferase; AST = aspartate aminotransferase.
a Consists of new onset of laboratory abnormality or worsening of baseline laboratory abnormality.

Mismatch Repair Deficient Recurrent or Advanced Endometrial Cancer: JEMPERLI as a Single Agent

The safety of JEMPERLI was evaluated in GARNET in 150 patients with advanced or recurrent dMMR EC who received at least 1 dose of JEMPERLI [see Clinical Studies (14.1)]. Patients received JEMPERLI 500 mg every 3 weeks for 4 cycles followed by 1,000 mg every 6 weeks as an intravenous infusion until disease progression or unacceptable toxicity. Patients with autoimmune disease that required systemic therapy within 2 years of treatment or a medical condition that required immunosuppression were ineligible. Among patients receiving JEMPERLI, 41% were exposed for >1 year and 23% were exposed for >2 years.

A fatal adverse reaction occurred in one patient (0.7%) who received JEMPERLI, due to concurrent immune-mediated encephalitis and urinary tract infection.

Serious adverse reactions occurred in 38% of patients receiving JEMPERLI. Serious adverse reactions in >2% of patients included urinary tract infection (4%), sepsis (3.3%), acute kidney injury (2.7%), and abdominal pain (2.7%).

JEMPERLI was permanently discontinued due to adverse reactions in 15 (10%) patients, including increased transaminases, sepsis, bronchitis, pneumonitis, rash, pruritus, pancreatitis, encephalitis, and nephritis. Dosage interruptions due to an adverse reaction occurred in 28% of patients who received JEMPERLI. Adverse reactions that required dosage interruption in >1% of patients who received JEMPERLI were anemia, diarrhea, asthenia, colitis, sepsis, and pneumonitis.

The most common adverse reactions (≥20%) were fatigue/asthenia, anemia, nausea, diarrhea, constipation, vomiting, and rash.

Table 5 summarizes the adverse reactions that occurred in ≥10% of patients with dMMR EC on JEMPERLI in GARNET.

Table 5. Adverse Reactions (≥10%) in Patients with dMMR Endometrial Cancer Who Received JEMPERLI in GARNET
Adverse Reaction | JEMPERLI; N = 150
Adverse Reaction | All Grades; % | Grade 3 or 4; %
General and administration site
Fatiguea; Pyrexia | 49; 13 | 3.3; 0
Blood and lymphatic system; Anemiab | 35 | 18
Gastrointestinal
Nausea | 32 | 0.7
Diarrhea | 29 | 2.7
Constipation | 23 | 0.7
Vomiting | 23 | 0.7
Skin and subcutaneous tissue; Rashc; Pruritus | 21; 19 | 0; 1.3
Infections; Urinary tract infection | 19 | 4
Metabolism and nutrition
Decreased appetite | 15 | 0
Respiratory, thoracic, and mediastinal
Cough | 15 | 0
Musculoskeletal and connective tissue
Myalgia | 10 | 0
Investigations; Increased transaminasesd | 13 | 4
Endocrine Disorders; Hypothyroidism | 11 | 0
dMMR = Mismatch Repair Deficient.
Toxicity was graded per National Cancer Institute Common Terminology Criteria for Adverse Events Version 4.03.
a Includes fatigue and asthenia.
b Includes anemia, decreased hemoglobin, iron deficiency, and iron deficiency anemia.
c Includes rash, rash maculo-papular, rash pruritic, erythema, and pemphigoid.
d Includes increased alanine aminotransferase, increased aspartate aminotransferase, increased transaminases, and
hypertransaminasemia.

Clinically relevant adverse reactions in <10% of patients who received JEMPERLI included:

Endocrine Disorders: Hyperthyroidism, adrenal insufficiency, hypophysitis.

Eye Disorders: Iridocyclitis, uveitis.

Gastrointestinal Disorders: Colitis, pancreatitis, enterocolitis, gastritis.

General Disorders and Administration Site Conditions: Chills.

Musculoskeletal and Connective Tissue Disorders: Immune-mediated myositis, immune-mediated arthritis.

Nervous System Disorders: Encephalitis.

Renal and Urinary Disorders: Nephritis.

Respiratory, Thoracic, and Mediastinal Disorders: Pneumonitis, interstitial lung disease.

Table 6 summarizes laboratory abnormalities worsening from baseline to Grade 3 or 4 in ≥1% of patients with dMMR EC on JEMPERLI in GARNET.

Table 6. Laboratory Abnormalities that Worsened from Baseline to Grade 3 or 4 Occurring in ≥1% of Patients with dMMR Endometrial Cancer Receiving JEMPERLI in GARNET
Laboratory Test | JEMPERLI; N = 150
Laboratory Test | All Gradesa; % | Grade 3 or 4a; %
Hematology
Decreased lymphocytes | 46 | 15
Decreased leukocytes; Decreased neutrophils | 21; 17 | 2; 2.7
Chemistry
Decreased albumin | 36 | 2.7
Increased creatinine | 33 | 3.4
Increased alkaline phosphatase | 31 | 2.7
Increased aspartate aminotransferase | 31 | 2
Increased alanine aminotransferase | 25 | 4.7
Electrolytes
Decreased sodium; Decreased magnesium; Decreased potassium | 29; 28; 22 | 5; 2; 2
Increased calcium | 8 | 2
dMMR = Mismatch Repair Deficient.
a Consists of new onset of laboratory abnormality or worsening of baseline laboratory abnormality.

Mismatch Repair Deficient Recurrent or Advanced Solid Tumors

The safety of JEMPERLI was investigated in 267 patients with recurrent or advanced dMMR solid tumors enrolled in GARNET [see Clinical Studies (14.2)]. Patients received JEMPERLI 500 mg every 3 weeks for 4 cycles followed by 1,000 mg every 6 weeks as an intravenous infusion until disease progression or unacceptable toxicity. Patients with autoimmune disease that required systemic therapy within 2 years of treatment or a medical condition that required immunosuppression were ineligible. The median duration of exposure to JEMPERLI was 25 weeks (range: 1 to 139 weeks).

Serious adverse reactions occurred in 34% of patients receiving JEMPERLI. Serious adverse reactions in >2% of patients included abdominal pain (3.7%), sepsis (2.6%), and acute kidney injury (2.2%). Fatal adverse reaction occurred in 1 patient who received JEMPERLI due to respiratory failure.

JEMPERLI was permanently discontinued due to adverse reactions in 9% patients; the most common adverse reaction (≥1%) leading to discontinuation was increased alanine aminotransferase (1.1%).

Dosage interruptions due to an adverse reaction occurred in 23% of patients who received JEMPERLI. Adverse reactions that required dosage interruption in ≥1% of patients who received JEMPERLI were anemia, pneumonitis, diarrhea, adrenal insufficiency, increased alanine aminotransferase, and increased aspartate aminotransferase.

The most common adverse reactions (≥20%) were fatigue/asthenia, anemia, diarrhea, and nausea.

Table 7 summarizes the adverse reactions that occurred in ≥10% of patients with dMMR recurrent or advanced solid tumors in GARNET.

Table 7. Adverse Reactions (≥10%) in Patients with dMMR Recurrent or Advanced Solid Tumors in GARNET
Adverse Reaction | JEMPERLI; N = 267
Adverse Reaction | All Grades; % | Grade 3 or 4; %
General and administration site
Fatiguea | 42 | 3.4
Pyrexia | 12 | 0
Blood and lymphatic system
Anemiab | 30 | 11
Gastrointestinal
Diarrhea | 25 | 1.5
Nausea | 22 | 0.4
Vomiting | 17 | 1.5
Constipation | 16 | 0.4
Skin and subcutaneous tissue
Pruritus | 15 | 0.4
Rashc | 14 | 0.4
Respiratory, thoracic, and mediastinal
Cough | 13 | 0
Metabolism and nutrition
Decreased appetite | 12 | 0.4
Investigations
Increased transaminasesd | 12 | 3
dMMR = Mismatch Repair Deficient.
Toxicity was graded per National Cancer Institute Common Terminology Criteria for Adverse Events Version 4.03.
a Includes fatigue and asthenia.
b Includes anemia, decreased hemoglobin, iron deficiency, and iron deficiency anemia.
c Includes rash, rash maculopapular, rash macular, rash erythematous, rash papular, erythema, toxic skin eruption, and pemphigoid.
d Includes increased alanine aminotransferase, increased aspartate aminotransferase, increased transaminases, and hypertransaminasemia.

Clinically relevant adverse reactions in <10% of patients who received JEMPERLI included:

Endocrine Disorders: Hypothyroidism, hyperthyroidism, adrenal insufficiency, hypophysitis, autoimmune thyroiditis.

Eye Disorders: Uveitis.

Gastrointestinal Disorders: Colitis, enterocolitis, enterocolitis hemorrhage, pancreatitis, acute pancreatitis.

General Disorders and Administration Site Conditions: Chills.

Injury, Poisoning, and Procedural Complications: Infusion related reaction.

Hepatobiliary Disorders: Hepatocellular injury.

Musculoskeletal and Connective Tissue Disorders: Myalgia.

Renal and Urinary Disorders: Nephritis, tubulointerstitial nephritis.

Respiratory, Thoracic, and Mediastinal Disorders: Pneumonitis, interstitial lung disease.

Table 8 summarizes laboratory abnormalities worsening from baseline to Grade 3 or 4 in ≥1% of patients with dMMR recurrent or advanced solid tumors in GARNET.

Table 8. Laboratory Abnormalities that Worsened from Baseline to Grade 3 or 4 Occurring in ≥1% of Patients with dMMR Recurrent or Advanced Solid Tumors in GARNET
Laboratory Test | JEMPERLI; N = 267
Laboratory Test | All Gradesa; % | Grade 3 or 4a; %
Hematology
Decreased lymphocytes | 33 | 7
Decreased leukocytes | 18 | 1.1
Decreased neutrophils | 12 | 1.5
Chemistry
Decreased albumin | 26 | 2.2
Increased alkaline phosphatase | 26 | 3.4
Increased aspartate aminotransferase | 26 | 1.5
Increased alanine aminotransferase | 22 | 1.9
Increased creatinine | 21 | 1.1
Increased total bilirubin | 7 | 1.5
Electrolytes
Decreased sodium | 21 | 4.9
Decreased magnesium | 16 | 1.1
Decreased potassium | 14 | 1.1
Increased potassium | 14 | 1.1
Increased calcium | 6 | 1.1
Increased magnesium | 4.1 | 1.5
Decreased calcium | 2.6 | 1.5
dMMR = Mismatch Repair Deficient.
a Consists of new onset of laboratory abnormality or worsening of baseline laboratory abnormality.

8 USE IN SPECIFIC POPULATIONS

8.1 Pregnancy

Risk Summary

Based on its mechanism of action, JEMPERLI can cause fetal harm when administered to a pregnant woman [see Clinical Pharmacology (12.1)]. There are no available data on the use of JEMPERLI in pregnant women. Animal studies have demonstrated that inhibition of the PD-1/PD-L1 pathway can lead to increased risk of immune-mediated rejection of the developing fetus resulting in fetal death (see). Human IgG4 immunoglobulins (IgG4) are known to cross the placental barrier; therefore, dostarlimab-gxly has the potential to be transmitted from the mother to the developing fetus. Advise women of the potential risk to a fetus.

In the U.S. general population, the estimated background risk of major birth defects and miscarriage in clinically recognized pregnancies is 2% to 4% and 15% to 20%, respectively.

Data

Animal Data: Animal reproduction studies have not been conducted with JEMPERLI to evaluate its effect on reproduction and fetal development. A central function of the PD-1/PD-L1 pathway is to preserve pregnancy by maintaining maternal immune tolerance to the fetus. In murine models of pregnancy, blockade of PD-L1 signaling has been shown to disrupt tolerance to the fetus and to result in an increase in fetal loss; therefore, potential risks of administering JEMPERLI during pregnancy include increased rates of abortion or stillbirth. As reported in the literature, there were no malformations related to the blockade of PD-1/PD-L1 signaling in the offspring of these animals; however, immune-mediated disorders occurred in PD-1 and PD-L1 knockout mice. Based on its mechanism of action, fetal exposure to dostarlimab-gxly may increase the risk of developing immune-mediated disorders or altering the normal immune response.

8.2 Lactation

Risk Summary

There is no information regarding the presence of dostarlimab-gxly in human milk or its effects on the breastfed child or on milk production. Maternal IgG is known to be present in human milk. The effects of local gastrointestinal exposure and limited systemic exposure in the breastfed child to JEMPERLI are unknown. Because of the potential for serious adverse reactions in a breastfed child, advise women not to breastfeed during treatment and for 4 months after the last dose of JEMPERLI.

8.3 Females and Males of Reproductive Potential

JEMPERLI can cause fetal harm when administered to a pregnant woman [see Use in Specific Populations (8.1)].

Pregnancy Testing

Verify pregnancy status in females of reproductive potential prior to initiating JEMPERLI [see Use in Specific Populations (8.1)].

Contraception

Females: Advise females of reproductive potential to use effective contraception during treatment with JEMPERLI and for 4 months after the last dose.

8.4 Pediatric Use

The safety and efficacy of JEMPERLI have not been established in pediatric patients.

8.5 Geriatric Use

In Combination with Carboplatin and Paclitaxel

Of the 241 patients treated with JEMPERLI in RUBY, 52.3% were younger than 65 years, 36.5% were aged 65 through 74 years, and 11.2% were 75 years or older. No overall differences in safety or effectiveness were observed between these patients and younger patients.

As a Single Agent

Of the 605 patients treated with JEMPERLI in GARNET, 51.6% were younger than 65 years, 36.9% were aged 65 through 74 years, and 11.5% were 75 years or older. No overall differences in safety or effectiveness were observed between these patients and younger patients.

11 DESCRIPTION

Dostarlimab-gxly is a programmed death receptor-1 (PD-1)–blocking IgG4 humanized monoclonal antibody. Dostarlimab‑gxly is produced in Chinese hamster ovary cells and has a calculated molecular weight of about 144 kDa.

JEMPERLI (dostarlimab-gxly) injection is a sterile, clear to slightly opalescent, colorless to yellow solution essentially free from visible particles. It is supplied as single-dose vials.

Each vial contains 500 mg of JEMPERLI in 10 mL of solution with a pH of 6. Each mL of solution contains 50 mg of dostarlimab-gxly, citric acid monohydrate (0.48 mg), L-arginine hydrochloride (21.07 mg), polysorbate 80 (0.2 mg), sodium chloride (1.81 mg), trisodium citrate dihydrate (6.68 mg), and Water for Injection, USP.

12 CLINICAL PHARMACOLOGY

12.1 Mechanism of Action

Binding of the PD-1 ligands, PD-L1 and PD-L2, to the PD-1 receptor found on T cells inhibits T-cell proliferation and cytokine production. Upregulation of PD-1 ligands occurs in some tumors, and signaling through this pathway can contribute to inhibition of active T-cell immune surveillance of tumors. Dostarlimab-gxly is a humanized monoclonal antibody of the IgG4 isotype that binds to the PD-1 receptor and blocks its interaction with PD-L1 and PD-L2, releasing PD-1 pathway-mediated inhibition of the immune response, including the anti-tumor immune response. In syngeneic mouse tumor models, blocking PD-1 activity resulted in decreased tumor growth.

12.2 Pharmacodynamics

The exposure-response relationship and time course of pharmacodynamic response for safety and effectiveness of dostarlimab-gxly have not been fully characterized.

Dostarlimab-gxly provides sustained target engagement as measured by direct PD-1 binding and stimulation of IL-2 production throughout the dosing interval at the recommended dosage.

12.3 Pharmacokinetics

The pharmacokinetics of dostarlimab-gxly as a single agent and in combination with carboplatin and paclitaxel were evaluated in patients with various solid tumors, including patients with EC. Mean Cmax, AUC0-inf, and AUC0-tau increased proportionally over the dose range of 1 to 10 mg/kg. The Cycle 1 mean (coefficient of variation [%CV]) Cmax and AUC0-tau of dostarlimab-gxly as a single agent were 171 mcg/mL (20%) and 35,730 mcg*h/mL (20%), respectively at the dosage of 500 mg once every 3 weeks and 309 mcg/mL (31%) and 95,820 mcg*h/mL (29%), respectively at the dosage of 1,000 mg every 6 weeks.

Distribution

The mean (%CV) volume of distribution of dostarlimab-gxly at steady state is approximately 5.8 L (15%).

Elimination

The mean terminal elimination half-life of dostarlimab-gxly at steady state is 23.5 days and its mean (%CV) clearance at steady state is 0.007 L/h (30%).

Metabolism: Dostarlimab-gxly is expected to be metabolized into small peptides and amino acids by catabolic pathways.

Specific Populations

No clinically significant differences in the pharmacokinetics of dostarlimab-gxly were observed based on age (24 to 86 years), sex, race/ethnicity (75% White, 2% Asian, and 5% African American), tumor type, and renal impairment based on the estimated creatinine clearance (eGFR ≥15 mL/min/1.73 m^2), and mild to moderate hepatic impairment [total bilirubin (TB) >ULN to 3 times ULN or AST>ULN to any AST].

Drug Interaction Studies

Dostarlimab exposure when administered in combination with carboplatin and paclitaxel was comparable to single agent exposure and there was no evidence to suggest a clinically relevant change of dostarlimab-gxly clearance over time in patients with recurrent or advanced EC.

12.6 Immunogenicity

The observed incidence of anti-drug antibodies is highly dependent on the sensitivity and specificity of the assay. Differences in assay methods preclude meaningful comparisons of the incidence of anti-drug antibodies in the studies described below with the incidence of anti-drug antibodies in other studies, including those of JEMPERLI or of other dostarlimab-gxly products.

The immunogenicity of dostarlimab-gxly was evaluated in RUBY at a dosage of 500 mg every 3 weeks for 6 cycles followed by 1,000 mg every 6 weeks thereafter; there was no formation of anti-drug antibodies and neutralizing antibodies in 225 patients receiving JEMPERLI at the recommended dosage.

The immunogenicity of dostarlimab-gxly was evaluated in GARNET at a dose of 500 mg every 3 weeks for 4 cycles followed by 1,000 mg every 6 weeks thereafter. Anti‑drug antibodies against dostarlimab-gxly were detected in 2.1% (8/384) of patients who received JEMPERLI at the recommended dosage. Neutralizing antibodies were detected in 1% (4/384) of patients.

Because of the small number of patients who developed anti-drug antibodies, the effect of immunogenicity on the pharmacokinetics, efficacy, and safety of dostarlimab-gxly is inconclusive.

13 NONCLINICAL TOXICOLOGY

13.1 Carcinogenesis, Mutagenesis, Impairment of Fertility

No studies have been performed to assess the potential of dostarlimab-gxly for carcinogenicity or genotoxicity.

Fertility studies have not been conducted with dostarlimab-gxly. In 1- and 3-month repeat‑dose toxicology studies in monkeys, there were no notable effects in the male and female reproductive organs; however, many animals in these studies were not sexually mature.

13.2 Animal Toxicology and/or Pharmacology

In animal models, inhibition of PD-L1/PD-1 signaling increased the severity of some infections and enhanced inflammatory responses. Mycobacterium tuberculosis-infected PD-1 knockout mice exhibit markedly decreased survival compared with wild-type controls, which correlated with increased bacterial proliferation and inflammatory responses in these animals. PD-1 blockade using a primate anti-PD-1 antibody was also shown to exacerbate M. tuberculosis infection in rhesus macaques. PD-L1 and PD-1 knockout mice and mice receiving PD-L1–blocking antibody have also shown decreased survival following infection with lymphocytic choriomeningitis virus.

14 CLINICAL STUDIES

14.1 Endometrial Cancer

In Combination with Carboplatin and Paclitaxel for the Treatment of Primary Advanced or Recurrent Endometrial Cancer

The efficacy of JEMPERLI in combination with carboplatin and paclitaxel, followed by JEMPERLI as a single agent, was evaluated in RUBY (NCT03981796), a randomized, multicenter, double-blind, placebo-controlled trial conducted in 494 patients with primary advanced or recurrent EC.

The trial enrolled patients with primary Stage III or Stage IV disease (per FIGO Staging Classification), including Stage IIIA to IIIC1 patients with evaluable or measurable disease, Stage IIIC1 patients with carcinosarcoma, clear cell, serous, or mixed histology regardless of presence of evaluable or measurable disease, Stage IIIC2 or Stage IV disease regardless of presence of evaluable or measurable disease. The trial also enrolled patients with first recurrent disease with a low potential for cure by radiation therapy or surgery alone or in combination, including patients who were naïve to systemic anticancer therapy or who had received prior neo-adjuvant/adjuvant systemic anticancer therapy and had a recurrence or disease progression ≥6 months after completing treatment.

Patients were randomized (1:1) to one of the following treatments arms:

- JEMPERLI 500 mg, carboplatin AUC 5 mg/mL/min, paclitaxel 175 mg/m^2 intravenously on Day 1 of each 21-day cycle for 6 cycles followed by JEMPERLI 1,000 mg intravenously every 6 weeks. JEMPERLI was administered prior to chemotherapy on Day 1.
- Placebo, carboplatin AUC 5 mg/mL/min, paclitaxel 175 mg/m^2 intravenously on Day 1 of each 21-day cycle for 6 cycles followed by placebo intravenously every 6 weeks.

Randomization was stratified by mismatch repair (MMR)/microsatellite instability (MSI) status, prior external pelvic radiotherapy, and disease status (recurrent, primary Stage III, or primary Stage IV). Treatment with JEMPERLI continued until disease progression, unacceptable toxicity, or a maximum of 3 years. Administration of JEMPERLI was permitted beyond disease progression (defined by Response Evaluation Criteria in Solid Tumors [RECIST] v1.1) if the patient was clinically stable and considered to be deriving clinical benefit by the investigator.

Assessment of tumor status was performed every 6 weeks through Week 25, every 9 weeks through Week 52 and every 12 weeks thereafter. The major efficacy outcomes were Progression-Free Survival (PFS) using RECIST v1.1 as assessed by investigator in the dMMR/MSI-H and overall populations, and Overall Survival (OS) in the overall population. Additional efficacy outcome measures included Objective Response Rate (ORR) per RECIST v1.1 as assessed by investigator and Duration of Response (DOR).

Among the 494 patients evaluated, the baseline characteristics were: median age 65 years (51% aged 65 years or older); 77% White, 12% Black, 3% Asian, 3% Hispanic or Latino; Eastern Cooperative Oncology Group (ECOG) Performance Status 0 (63%) or 1 (37%); and primary stage III (18%); primary stage IV (34%) and recurrent EC (48%). Overall, 24% were dMMR/MSI-H tumors and 76% were mismatch repair proficient (MMRp)/microsatellite stable (MSS) tumors.

Efficacy results are presented in Table 9 and Figures , and . Treatment with JEMPERLI in combination with carboplatin and paclitaxel demonstrated statistically significant improvements in OS in the overall population and PFS in both the dMMR/MSI-H and overall population versus placebo in combination with carboplatin and paclitaxel. Pre-specified exploratory analyses of PFS and OS were performed in patients with MMRp/MSS EC.

Table 9. Efficacy Results of Endometrial Cancer Population in RUBY
Endpoint | Overall Population |  | dMMR/MSI-H Population
 | JEMPERLI with Carboplatin and Paclitaxel; N = 245 | Placebo with Carboplatin and Paclitaxel; N = 249 | JEMPERLI with Carboplatin and Paclitaxel; N = 60 | Placebo withCarboplatin and Paclitaxel; N = 62
Overall Survival (OS)
Number (%) of patients with event | 109 (44) | 144 (58) | 15 (25) | 35 (56)
Median in months; (95% CI) | 44.6; (32.6, NR) | 28.2; (22.1, 35.6) | NR; (NR, NR) | 30.8; (18.7, NR)
Hazard ratio (95% CI)a | 0.69 (0.54, 0.89) |  | 0.34 (0.18, 0.62)
P-valueb | 0.002 |  | Not tested
Progression-Free Survival (PFS)
Number (%) of patients with event | 135 (55) | 177 (71) | 23 (38) | 47 (76)
Median in months; (95% CI) | 11.8; (9.6, 17.1) | 7.9; (7.6, 9.5) | 30.3; (11.8, NR) | 7.7; (5.6, 9.7)
Hazard ratio (95% CI)a | 0.64 (0.51, 0.80) |  | 0.29 (0.17, 0.50)
P-valueb | <0.0001 |  | <0.0001
Objective Response Rate (ORR)c
Number of participants with measurable disease at baseline (n) | 172 | 185 | 42 | 45
ORR (95% CI) | 68%; (60, 75) | 57%; (50, 65) | 74%; (58, 86) | 62%; (47, 76)
Complete response rate | 20% | 12% | 26% | 11%
Partial response rate | 48% | 45% | 48% | 51%
Duration of Response (DOR)c
Median in months (range) | 10.8; (1.3+, 28.9+) | 6.4; (1.4+, 27.2+) | NR; (3.4, 28.3+) | 5.4; (2.7, 27.2+)
dMMR = Mismatch Repair Deficient; MSI-H = Microsatellite Instability-High; NR = Not Reached; + = ongoing at last assessment.
a Based on stratified Cox regression model.
b One-sided P-value based on stratified log-rank test.
c Confirmed responses.

In patients with MMRp/MSS EC (n = 372), the OS hazard ratio (HR) was 0.82 (95% CI: 0.62, 1.08) with a median OS of 32.5 (95% CI: 28.6, NR) months for JEMPERLI in combination with carboplatin and paclitaxel versus 28.2 (95% CI: 21.9, 36.1) months for placebo in combination with carboplatin and paclitaxel. The PFS HR was 0.78 (95% CI: 0.60, 1.00) with a median PFS of 9.8 (95% CI: 9.0, 12.6) months for JEMPERLI in combination with carboplatin and paclitaxel (n = 185) versus 7.9 (95% CI: 7.6, 9.8) months for placebo in combination with carboplatin and paclitaxel (n = 187).

Figure 1. Kaplan-Meier Curve for Overall Survival in Patients (Overall Population) with Endometrial Cancer in RUBY

Figure 2. Kaplan-Meier Curve for Progression-Free Survival in Patients (Overall Population) with Endometrial Cancer in RUBY

Figure 3. Kaplan-Meier Curve for Progression-Free Survival in Patients with dMMR/MSI-H Endometrial Cancer in RUBY

dMMR = Mismatch Repair Deficient; MSI-H = Microsatellite Instability High.

As a Single Agent for the Treatment of dMMR Recurrent or Advanced Endometrial Cancer

The efficacy of JEMPERLI as a single agent was evaluated in the GARNET trial (NCT02715284), a multicenter, multicohort, open-label trial conducted in patients with advanced solid tumors. The efficacy population consisted of a cohort of 141 patients with dMMR recurrent or advanced EC who had progressed on or after treatment with a platinum‑containing regimen. Patients with prior treatment with PD‑1/PD‑L1–blocking antibodies or other immune checkpoint inhibitor therapy and patients with autoimmune disease that required systemic therapy with immunosuppressant agents within 2 years were excluded from the trial.

Patients received JEMPERLI 500 mg intravenously every 3 weeks for 4 doses followed by 1,000 mg intravenously every 6 weeks. Treatment continued until disease progression or unacceptable toxicity. The major efficacy outcome measures were ORR and DOR as assessed by blinded independent central review (BICR) according to the RECIST v 1.1.

The baseline characteristics were: median age 65 years (53% aged 65 years or older); 77% White, 4% Asian, 3% Black, 4% Hispanic or Latino; and Eastern Cooperative Oncology Group Performance Status 0 (38%) or 1 (62%).

The most common histology seen was endometrioid carcinoma type 1 (65%), Grade 3 endometrioid (15%), followed by serous (5%), mixed (5%) and undifferentiated (2.8%).

All patients with dMMR EC had received prior anticancer treatment, with 89% of patients receiving prior anticancer surgery and 71% receiving prior anticancer radiotherapy. Sixty-three percent of patients had one prior line of anticancer treatment and 37% had two or more prior lines. Forty-eight patients (34%) received treatment only in the neoadjuvant or adjuvant setting before participating in the study.

The dMMR tumor status was retrospectively confirmed using the VENTANA MMR RxDx Panel assay.

Efficacy results are presented in Table 10.

Table 10. Efficacy Results of dMMR Endometrial Cancer Population in GARNET
Endpoint | JEMPERLI; N = 141
Overall response ratea
ORR (95% CI) | 45.4% (37.0, 54.0)
Complete response rate | 15.6%
Partial response rate | 29.8%
Duration of responseb
Median in months | Not reached
(range) | (1.2+, 52.8+)
Patients with duration ≥12 months | 85.9%
Patients with duration >24 months | 54.7%
dMMR = Mismatch Repair Deficient; + = ongoing at last assessment.
a Based on confirmed response by blinded independent central review.
b Median follow up for duration of response was 27.9 months measured from time of first response.

14.2 Mismatch Repair Deficient Recurrent or Advanced Solid Tumors

The efficacy of JEMPERLI as a single agent was evaluated in GARNET (NCT02715284), a non‑randomized, multicenter, open-label, multicohort trial. The efficacy population consisted of a cohort of 209 patients with dMMR recurrent or advanced solid tumors who progressed following systemic therapy and had no satisfactory alternative treatment options. Patients with dMMR EC must have progressed on or after treatment with a platinum-containing regimen. Patients with dMMR colorectal cancer must have progressed after or been intolerant to a fluoropyrimidine, oxaliplatin, and irinotecan.

Patients with prior treatment with PD‑1/PD‑L1–blocking antibodies or other immune checkpoint inhibitor therapy and patients with autoimmune disease that required systemic therapy with immunosuppressant agents within 2 years were excluded from the trial.

Patients received JEMPERLI 500 mg intravenously every 3 weeks for 4 doses followed by 1,000 mg intravenously every 6 weeks. Treatment continued until disease progression or unacceptable toxicity.

The major efficacy outcome measures were ORR and DOR as determined by a BICR according to RECIST v 1.1.

The baseline characteristics were female (77%); median age 63 years (47% aged 65 years or older); 63% White, 3% Asian, 2% Black; and Eastern Cooperative Oncology Group Performance Status 0 (39%) or 1 (61%).

At time of trial entry, 97.2% of patients (103/106) with non-endometrial dMMR solid tumors had Stage IV disease, and 68.0% (70/103) of patients with dMMR endometrial tumors had FIGO Stage IV disease.

Approximately 43% of patients had received 1 prior line of systemic anticancer treatment, 36% had received 2 prior lines, and 21% had received 3 or more prior lines.

The dMMR tumor status was retrospectively confirmed using the VENTANA MMR RxDx Panel assay.

Efficacy results are presented in Tables 11 and 12.

Table 11. Efficacy Results of dMMR Recurrent or Advanced Solid Tumors in GARNET
Endpoint | JEMPERLI; N = 209
Overall response ratea
ORR (95% CI) | 41.6% (34.9, 48.6)
Complete response rate | 9.1%
Partial response rate | 32.5%
Duration of responseb
Median in months | 34.7
(range) | 2.6, 35.8+
Patients with duration ≥6 months | 95.4%
dMMR = Mismatch Repair Deficient; + = ongoing at last assessment.
a Based on confirmed response by blinded independent central review.
b Median follow-up for duration of response was 17.5 months measured from time of first response.

Table 12. Efficacy Results of dMMR Tumor Types in GARNET
Tumor Type | Patients; N | ORR; (per RECIST v 1.1) |  | DOR
Tumor Type | Patients; N | n (%) | 95% CIa | Range (months)
EC | 103 | 46 (44.7) | (34.9, 54.8) | 2.6, 35.8+
non-EC | 106 | 41 (38.7) | (29.4, 48.6) | 5.6, 30.1+
CRC | 69 | 25 (36.2) | (25.0, 48.7) | 5.6, 30.1+
Small intestinal cancer | 12 | 4 (33.3) | (9.9, 65.1) | 11.1+, 28.0+
Gastric cancers | 8 | 3 (37.5) | (8.5, 75.5) | 8.4+, 17.5
Pancreatic carcinoma | 4 | 0 (0.0) | (0.0, 60.2) | NA
Biliary neoplasm | 2 | CR, CR | NA | 8.4+, 13.5+
Liver cancer | 2 | PR, PD | NA | 13.8+
Ovarian cancer | 2 | PR, SD | NA | 25.1+
Adrenal cortical | 1 | PR | NA | 19.5+
Breast cancer | 1 | CR | NA | 16.8+
Esophageal cancer | 1 | PD | NA | NA
Genital neoplasm malignant female | 1 | PR | NA | 22.2+
Pleural | 1 | PR | NA | 15.2+
Renal cell carcinoma | 1 | SD | NA | NA
Unknown origin | 1 | PR | NA | 20.4+
CR = complete response; CRC = colorectal cancer; dMMR = Mismatch Repair Deficient; DOR = Duration of Response; EC = endometrial cancer; ORR = Overall Response Rate; PD = progressive disease; PR = partial response; SD = stable disease; + = ongoing at last assessment.
a Exact, 2-sided 95% CI for binomial proportion.

16 HOW SUPPLIED/STORAGE AND HANDLING

JEMPERLI (dostarlimab-gxly) injection is a clear to slightly opalescent, colorless to yellow solution supplied in a carton containing one 500 mg/10 mL (50 mg/mL), single-dose vial (NDC 0173-0898-03).

Store vial refrigerated at 2°C to 8°C (36°F to 46°F) in original carton to protect from light. Do not freeze or shake.

17 PATIENT COUNSELING INFORMATION

Advise the patient to read the FDA-approved patient labeling (Medication Guide).

Immune-Mediated Adverse Reactions

Inform patients of the risk of immune-mediated adverse reactions that may be severe or fatal, may occur after discontinuation of treatment, and may require corticosteroid or other treatment and interruption or discontinuation of JEMPERLI. These reactions may include:

- Pneumonitis: Advise patients to contact their healthcare provider immediately for new or worsening cough, chest pain, or shortness of breath [see Warnings and Precautions (5.1)].
- Colitis: Advise patients to contact their healthcare provider immediately for diarrhea or severe abdominal pain [see Warnings and Precautions (5.1)].
- Hepatitis: Advise patients to contact their healthcare provider immediately for jaundice, severe nausea or vomiting, or easy bruising or bleeding [see Warnings and Precautions (5.1)].
- Immune-mediated endocrinopathies: Advise patients to contact their healthcare provider immediately for signs or symptoms of hypothyroidism, hyperthyroidism, thyroiditis, adrenal insufficiency, hypophysitis, or type 1 diabetes mellitus [see Warnings and Precautions (5.1)].
- Nephritis: Advise patients to contact their healthcare provider immediately for signs or symptoms of nephritis [see Warnings and Precautions (5.1)].
- Severe skin reactions: Advise patients to contact their healthcare provider immediately for any signs or symptoms of severe skin reactions, SJS, TEN, or DRESS [see Warnings and Precautions (5.1)].
- Other immune-mediated adverse reactions:
  - Advise patients that immune-mediated adverse reactions can occur and may involve any organ system, and to contact their healthcare provider immediately for any new signs or symptoms [see Warnings and Precautions (5.1)].
  - Advise patients of the risk of solid organ transplant rejection and to contact their healthcare provider immediately for signs or symptoms of organ transplant rejection [see Warnings and Precautions (5.1)].

Infusion-Related Reactions

- Advise patients to contact their healthcare provider immediately for signs or symptoms of infusion-related reactions [see Warnings and Precautions (5.2)].

Complications of Allogeneic HSCT

- Advise patients of the risk of post-allogeneic hematopoietic stem cell transplantation complications [see Warnings and Precautions (5.3)].

Embryo-Fetal Toxicity

- Advise females of reproductive potential of the potential risk to a fetus and to inform their healthcare provider of a known or suspected pregnancy [see Warnings and Precautions (5.4), Use in Specific Populations (8.1, 8.3)].
- Advise females of reproductive potential to use effective contraception during treatment with JEMPERLI and for 4 months after the last dose [see Warnings and Precautions (5.4), Use in Specific Populations (8.1, 8.3)].

Lactation

- Advise women not to breastfeed during treatment with JEMPERLI and for 4 months after the last dose [see Use in Specific Populations (8.2)].

Trademarks are owned by or licensed to the GSK group of companies.

Manufactured by:

GlaxoSmithKline LLC

Philadelphia, PA 19104

U.S. License No. 1727

Distributed by:

GlaxoSmithKline

Durham, NC 27701

©2025 GSK group of companies or its licensor.

JMP:8PI

MEDICATION GUIDE

JEMPERLI (jem-PER-lee)

(dostarlimab-gxly)

injection

What is the most important information I should know about JEMPERLI?

JEMPERLI is a medicine that may treat certain cancers by working with your immune system. JEMPERLI can cause your immune system to attack normal organs and tissues in any area of your body and can affect the way they work. These problems can sometimes become severe or life-threatening and can lead to death. You can have more than one of these problems at the same time. These problems may happen anytime during treatment or even after your treatment has ended.

Call or see your healthcare provider right away if you develop any new or worsening signs or symptoms, including:

Lung problems.

- cough

- shortness of breath

- chest pain

Intestinal problems.

- diarrhea or more bowel movements than usual
- stools that are black, tarry, sticky, or have blood or mucus
- severe stomach-area (abdomen) pain or tenderness

Liver problems.

- yellowing of your skin or the whites of your eyes
- severe nausea or vomiting
- pain on the right side of your stomach-area (abdomen)

- dark urine (tea colored)
- bleeding or bruising more easily than usual

Hormone gland problems.

- headaches that will not go away or unusual headaches
- eye sensitivity to light
- eye problems
- rapid heartbeat
- increased sweating
- extreme tiredness
- weight gain or weight loss
- feeling more hungry or thirsty than usual

- urinating more often than usual
- hair loss
- feeling cold
- constipation
- your voice gets deeper
- dizziness or fainting
- changes in mood or behavior, such as decreased sex drive, irritability, or forgetfulness

Kidney problems.

- change in the amount or color of your urine
- blood in your urine

- swelling in your ankles
- loss of appetite

Skin problems.

- rash
- itching
- skin blistering or peeling
- swollen lymph nodes

- painful sores or ulcers in your mouth or in your nose, throat, or genital area
- fever or flu-like symptoms

Problems can also happen in other organs and tissues. These are not all of the signs and symptoms of immune system problems that can happen with JEMPERLI. Call or see your healthcare provider right away for any new or worse signs or symptoms.

- chest pain, irregular heartbeat, shortness of breath, swelling of ankles
- confusion, sleepiness, memory problems, changes in mood or behavior, stiff neck, balance problems, tingling or numbness of the arms or legs
- double vision, blurry vision, sensitivity to light, eye pain, changes in eyesight
- persistent or severe muscle pain or weakness, muscle cramps
- low red blood cells, bruising

Infusion reactions that can sometimes be severe or life-threatening. Signs and symptoms of infusion reactions may include:

- chills or shaking
- itching or rash
- flushing
- shortness of breath or wheezing

- dizziness
- feel like passing out
- fever
- back or neck pain

Rejection of a transplanted organ. Your healthcare provider should tell you what signs and symptoms you should report and monitor you, depending on the type of organ transplant that you have had.

Complications, including graft-versus-host-disease (GVHD), in people who have received a bone marrow (stem cell) transplant that uses donor stem cells (allogeneic). These complications can be serious and can lead to death. These complications may happen if you underwent transplantation either before or after being treated with JEMPERLI. Your healthcare provider will monitor you for these complications.

Getting medical treatment right away may help keep these problems from becoming more serious.

Your healthcare provider will check you for these problems during treatment with JEMPERLI. Your healthcare provider may treat you with corticosteroid or hormone replacement medicines. Your healthcare provider may also need to delay or completely stop treatment with JEMPERLI, if you have severe side effects.

What is JEMPERLI?

JEMPERLI is a prescription medicine used to treat adults with:

- a kind of uterine cancer called endometrial cancer (EC)
○JEMPERLI may be used in combination with the chemotherapy medicines carboplatin and paclitaxel, and then after that, JEMPERLI may be used alone:
  1. when your cancer has spread outside your uterus (advanced) or,
  2. your cancer has returned.
○JEMPERLI may be used alone:
  1. when a laboratory test shows that your tumor is mismatch repair deficient (dMMR), and
  2. your cancer has returned, or it has spread (advanced EC), and
  3. you have received chemotherapy that contains platinum, and it did not work or is no longer working, and
  4. your cancer cannot be treated by surgery or radiation.
- a kind of cancer that is shown by laboratory test to be mismatch repair deficient (dMMR) solid tumor. JEMPERLI may be used alone to treat:
○cancer that has returned or has spread (advanced cancer) and,
○has progressed during treatment or after treatment, and you have no satisfactory treatment options.

It is not known if JEMPERLI is safe and effective in children.

Before receiving JEMPERLI, tell your healthcare provider about all of your medical conditions, including if you:

- have immune system problems, such as Crohn’s disease, ulcerative colitis, or lupus.
- have received an organ transplant.
- have received or plan to receive a stem cell transplant that uses donor stem cells (allogeneic).
- have received radiation treatment to your chest area.
- have a condition that affects your nervous system, such as myasthenia gravis or Guillain-Barré syndrome.
- are pregnant or plan to become pregnant. JEMPERLI can harm your unborn baby.
Females who are able to become pregnant:
○Your healthcare provider will do a pregnancy test before you start treatment with JEMPERLI.
○You should use an effective method of birth control during your treatment and for 4 months after your last dose of JEMPERLI. Talk to your healthcare provider about birth control methods that you can use during this time.
○Tell your healthcare provider right away if you become pregnant or think you may be pregnant during treatment with JEMPERLI.
- are breastfeeding or plan to breastfeed. It is not known if JEMPERLI passes into your breast milk. Do not breastfeed during treatment and for 4 months after your last dose of JEMPERLI.

Tell your healthcare provider about all the medicines you take, including prescription and over-the-counter medicines, vitamins, and herbal supplements.

How will I receive JEMPERLI?

- Your healthcare provider will give you JEMPERLI into your vein through an intravenous (IV) line over 30 minutes.
- When JEMPERLI is used in combination with carboplatin and paclitaxel, JEMPERLI is usually given every 3 weeks for the first 6 doses. Beginning 3 weeks later, it is usually given alone every 6 weeks.
- When JEMPERLI is used alone to treat dMMR recurrent or advanced EC and dMMR recurrent or advanced solid tumors, it is usually given every 3 weeks for the first 4 doses. Beginning 3 weeks later, it is usually given every 6 weeks.
- Your healthcare provider will decide how many treatments you need.
- Your healthcare provider will do blood tests to check you for side effects.
- If you miss any appointments, call your healthcare provider as soon as possible to reschedule your appointment.

What are the possible side effects of JEMPERLI?

JEMPERLI can cause serious side effects.

- See “What is the most important information I should know about JEMPERLI?”

The most common side effects of JEMPERLI when given with carboplatin and paclitaxel in people with EC include:

- nerve problems in your arms, hands, legs, and feet
- tiredness
- nausea
- hair loss

- joint pain
- rash
- constipation
- diarrhea
- stomach-area (abdomen) pain

- shortness of breath
- decreased appetite
- urinary tract infections
- vomiting

The most common side effects of JEMPERLI in people with dMMR solid tumors (including EC) when used alone include:

- tiredness and weakness
- low red blood cell count (anemia)

- diarrhea
- nausea

- constipation
- vomiting

These are not all of the possible side effects of JEMPERLI. Call your doctor for medical advice about side effects. You may report side effects to FDA at 1-800-FDA-1088.

General information about the safe and effective use of JEMPERLI.

Medicines are sometimes prescribed for purposes other than those listed in a Medication Guide. If you would like more information about JEMPERLI, talk with your healthcare provider. You can ask your pharmacist or healthcare provider for information about JEMPERLI that is written for healthcare professionals.

What are the ingredients in JEMPERLI?

Active ingredient: dostarlimab-gxly

Inactive ingredients: citric acid monohydrate, L-arginine hydrochloride, polysorbate 80, sodium chloride, trisodium citrate dihydrate, and Water for Injection.

Trademarks are owned by or licensed to the GSK group of companies.

Manufactured by:

GlaxoSmithKline LLC, Philadelphia, PA 19104, U.S. License No. 1727

Distributed by:

GlaxoSmithKline, Durham, NC 27701

©2024 GSK group of companies or its licensor.

JMP:5MG

For more information, call 1-888-825-5249 or go to www.gsk.com.

This Medication Guide has been approved by the U.S. Food and Drug Administration. Revised: August 2024

PACKAGE LABEL

PRINCIPAL DISPLAY PANEL

NDC 0173-0898-03

Jemperli

(dostarlimab-gxly) Injection

500 mg/10 mL

(50 mg/mL)

gsk

For Intravenous Infusion after Dilution

Single-Dose Vial

Rx only

Dispense the enclosed Medication Guide to each patient

©2020 GSK group of companies or its licensor.

Rev. 3/23

PCR-0022923